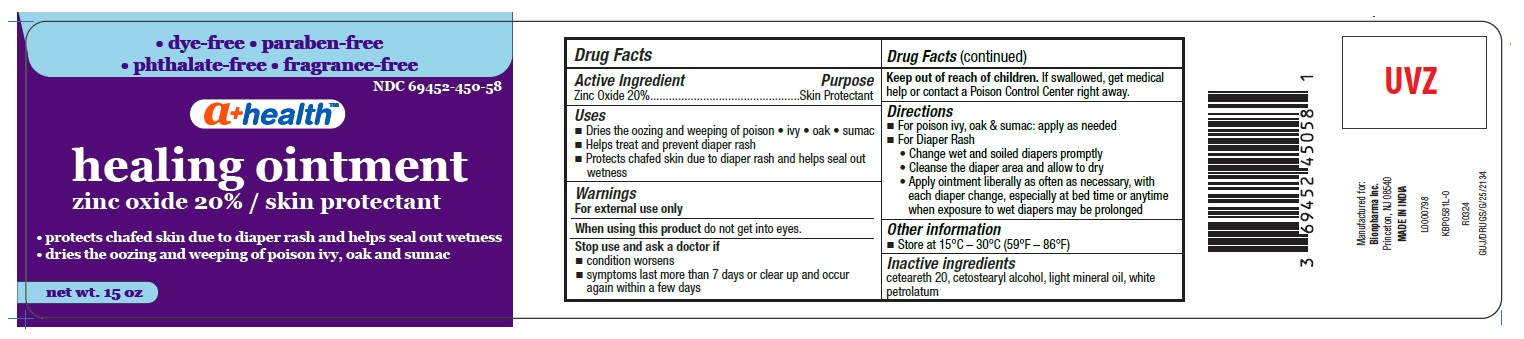 DRUG LABEL: zinc oxide 20%
NDC: 69452-450 | Form: OINTMENT
Manufacturer: Bionpharma Inc
Category: otc | Type: HUMAN OTC DRUG LABEL
Date: 20240418

ACTIVE INGREDIENTS: ZINC OXIDE 20 g/100 g
INACTIVE INGREDIENTS: CETETH-20; CETOSTEARYL ALCOHOL; LIGHT MINERAL OIL; WHITE PETROLATUM

Zinc Oxide 20%, A+ Health, Made in India

Active ingredient

Zinc Oxide 20 %

Purpose

Skin Protectant

Uses

■ Dries the oozing and weeping of poison • ivy • oak • sumac
■ Helps treat and prevent diaper rash
■ Protects chafed skin due to diaper rash and helps seal out wetness

Warnings

For external use only

When using this product

do not get into eyes.

Stop use and ask a doctor if

■ condition worsens
■ symptoms last more than 7 days or clear up and occur again within a few days

Keep out of reach of children.

If swallowed, get medical help or contact a Poison Control Center right away.

Directions

■ For poison ivy, oak & sumac: apply as needed

■ For Diaper Rash

- Change wet and soiled diapers promptly
- Cleanse the diaper area and allow to dry
- Apply ointment liberally as often as necessary, with each diaper change, especially at bed time or anytime when exposure to wet diapers may be prolonged

Other information

■ Store at 15°C – 30°C (59°F – 86°F)

Inactive ingredients

ceteareth 20, cetostearyl alcohol, light mineral oil, white petrolatum

Manufactured for:
Bionpharma Inc.
Princeton, NJ 08540
MADE IN INDIA

L0000798

KBP0581L-0

R0324
GUJ/DRUGS/G/25/2134

PACKAGE LABEL

NDC 69452-450-58

• dye-free • paraben-free

• phthalate-free • fragrance-free

a+ healthTM

healing ointment

zinc oxide 20% / skin protectant
• protects chafed skin due to diaper rash and helps seal out wetness
• dries the oozing and weeping of poison ivy, oak and sumac

net wt. 15 oz